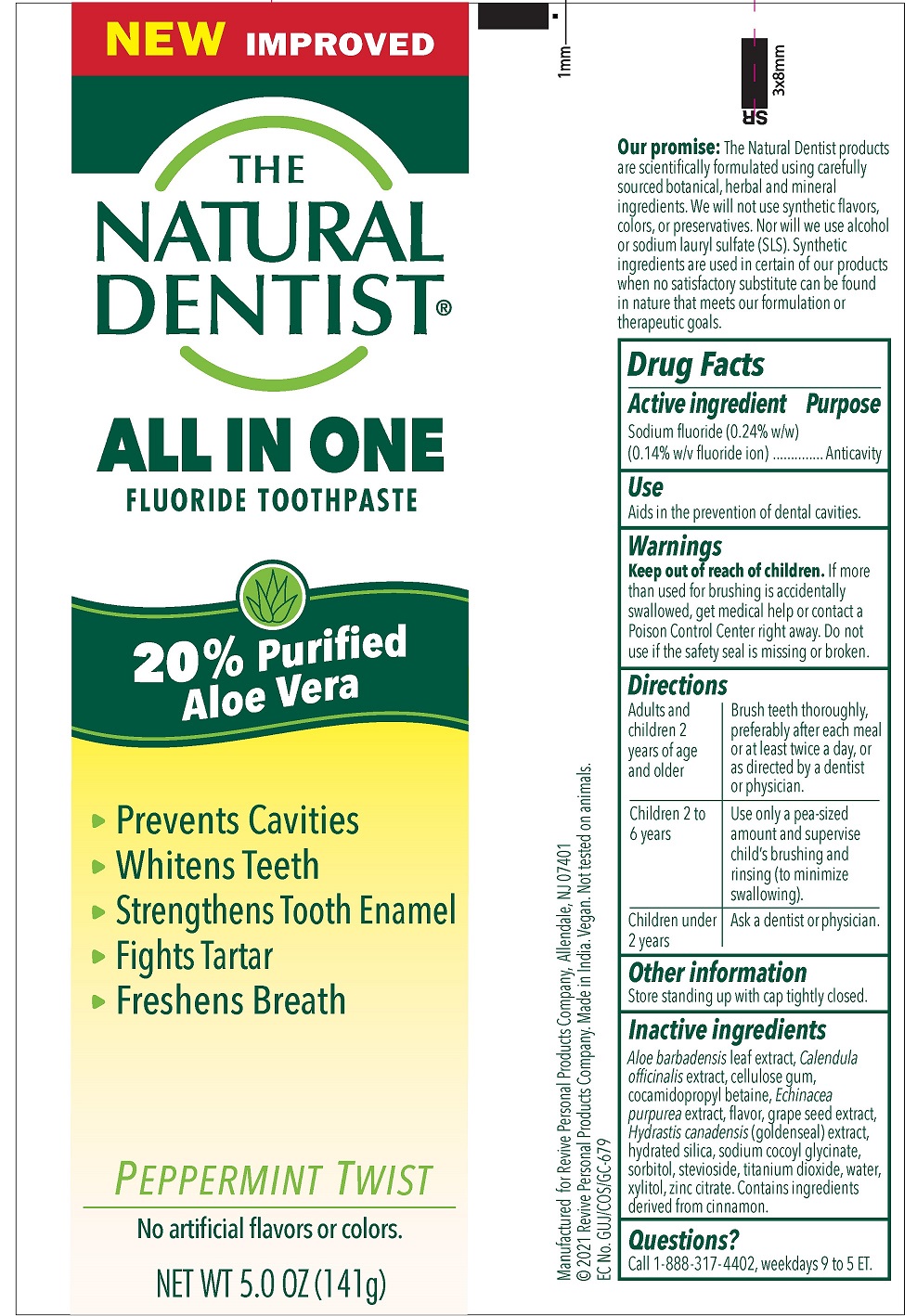 DRUG LABEL: Peppermint Twist
NDC: 34362-0237 | Form: PASTE, DENTIFRICE
Manufacturer: Caldwell Health LLC
Category: otc | Type: HUMAN OTC DRUG LABEL
Date: 20240117

ACTIVE INGREDIENTS: SODIUM FLUORIDE 0.243 g/100 g
INACTIVE INGREDIENTS: GLYCERIN; HYDRATED SILICA; SORBITOL; WATER; XYLITOL; ALOE VERA LEAF; COCAMIDOPROPYL BETAINE; SODIUM COCOYL GLYCINATE; CARBOXYMETHYLCELLULOSE SODIUM, UNSPECIFIED FORM; TITANIUM DIOXIDE; ECHINACEA ANGUSTIFOLIA; GOLDENSEAL; CALENDULA OFFICINALIS FLOWER; XANTHAN GUM; CITRIC ACID MONOHYDRATE; ZINC CITRATE; CITRUS MAXIMA SEED

The Natural Dentist All in One Toothpaste

Drug Facts

Active ingredient

Sodium fluoride (0.24%) (0.15% w/v fluoride ion)

Purpose

Anticavity

Use

Aids in the prevention of dental cavities.

Warnings

Keep out of reach of children. If more than used for brushing is accidentally swallowed, get medical help or contact a Poison Control Center right away. Do not use if the safety seal is missing or broken.

Directions

Adults and children 2 years of age and older | Brush teeth thoroughly, preferably after each meal or at least twice or as directed by a dentist or physician.
Children 2 to 6 years | Use only a pea-sized amount and supervise child's brushing and rinsing (to minimize swallowing).
Children under 2 years | Ask a dentist or physician.

Other information

Store standing up with cap tightly closed.

INACTIVE INGREDIENT

Inactive ingredients Glycerin, hydrated silica, sorbitol, water, xylitol, Aloe barbadensis leaf juice, cocamidopropyl betaine, sodium cocoylglycinate, cellulose gum, titanium dioxide, Echinacea angustifolia extract, natural flavors (contains Cinnamomum cassie leaf oil), Hydrastis canadensis (goldenseal) extract, Calendula officinalis extract, xanthan gum, citric acid, zinc citrate, Citrus grandis (grapefruit) seed extract.

QUESTIONS

Questions? Call 1-888-317-4402, weekdays 9 to 5 ET.

Manufactured for Revive Personal Products Company,

Allendale, NJ 07401

© 2018 Revive Personal Products Company.
Made in USA. Vegan. Not tested on animals.

PACKAGE LABEL

NO SLS!

THE NATURAL DENTIST

ALL IN ONE

FLUORIDE TOOTHPASTE

with Purified Aloe Vera

- Prevents Cavities
- Whitens Teeth
- Strengthens Tooth Enamel
- Fights Tartar
- Freshens Breath

PEPPERMINT TWIST

NET WT. 5.0 OZ (141g)